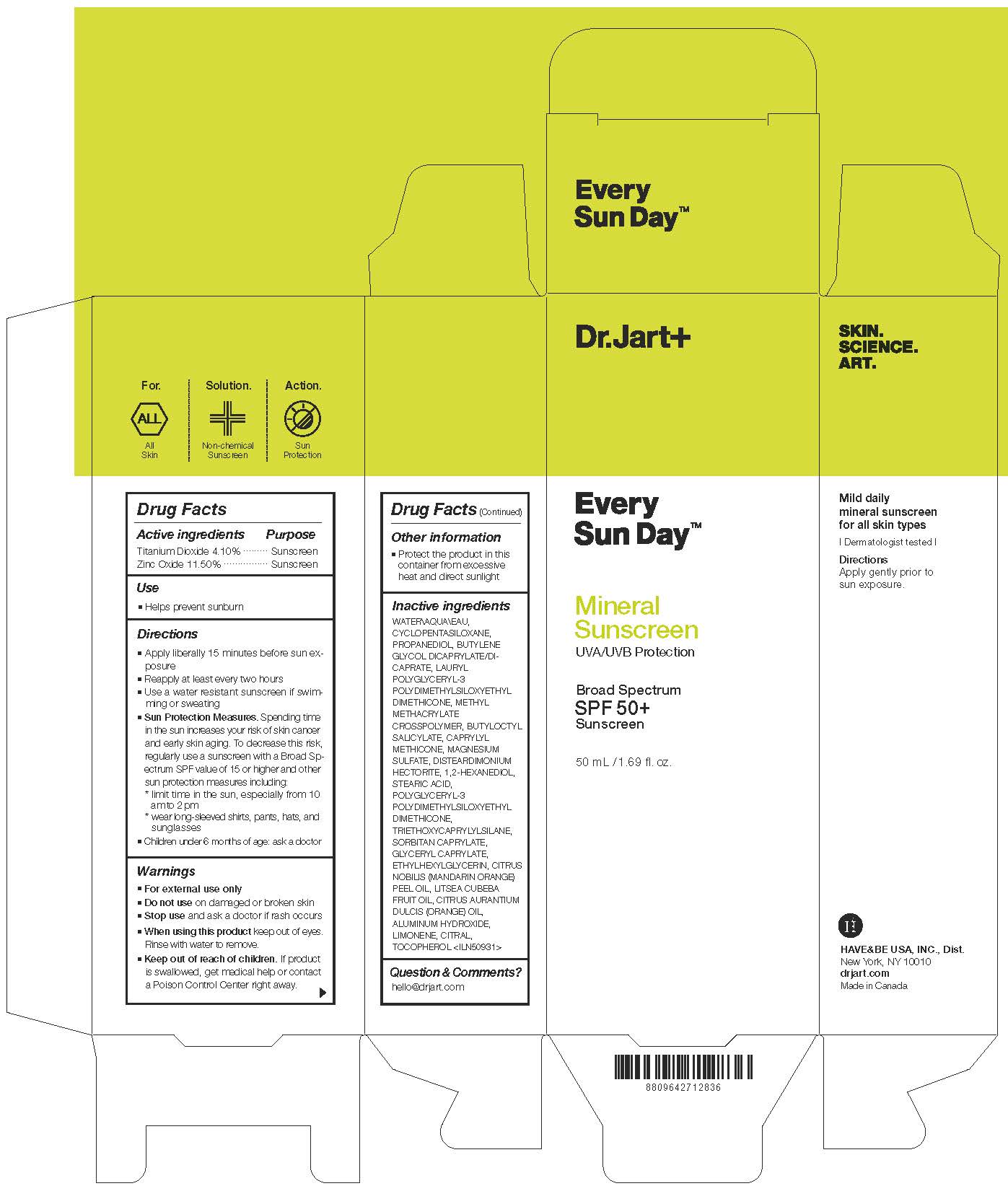 DRUG LABEL: DR.JART EVERY SUN DAY MINERAL SUN SCREEN
NDC: 49404-306 | Form: CREAM
Manufacturer: Have & Be Co., Ltd.
Category: otc | Type: HUMAN OTC DRUG LABEL
Date: 20250206

ACTIVE INGREDIENTS: TITANIUM DIOXIDE 41 mg/1 mL; ZINC OXIDE 115 mg/1 mL
INACTIVE INGREDIENTS: BUTYLENE GLYCOL DICAPRYLATE/DICAPRATE; CYCLOMETHICONE 5; ALUMINUM HYDROXIDE; TOCOPHEROL; SORBITAN MONOCAPRYLATE; CAPRYLYL TRISILOXANE; BUTYLOCTYL SALICYLATE; WATER; MAGNESIUM SULFATE, UNSPECIFIED; ORANGE OIL; LIMONENE, (+)-; DISTEARDIMONIUM HECTORITE; TRIETHOXYCAPRYLYLSILANE; ETHYLHEXYLGLYCERIN; METHYL METHACRYLATE/GLYCOL DIMETHACRYLATE CROSSPOLYMER; CITRAL; STEARIC ACID; GLYCERYL CAPRYLATE; 1,2-HEXANEDIOL; MANDARIN OIL; LITSEA OIL; PROPANEDIOL; POLYGLYCERYL-3 POLYDIMETHYLSILOXYETHYL DIMETHICONE (4000 MPA.S)

DR.JART EVERY SUN DAY MINERAL SUN SCREEN

Active ingredients

Titanium Dioxide 4.10%
Zinc Oxide 11.50%

Purpose

Sunscreen

Use

Helps prevent sunburn

Wanings

For external use only

Do not use

on damaged or broken skin

When using this product

keep out of eyes. Rinse with water to remove.

Stop use

and ask a doctor if rash occurs

Keep out of reach of children.

If product is swallowed, get medical help or contact a Poison Control Center right away.

Directions

Apply liberally 15 minutes before sun exposure

Reapply at least every two hours
■ Use a water resistant sunscreen if swim- ming or sweating
■ Sun Protection Measures. Spending time in the sun increases your risk of skin cancer and early skin aging. To decrease this risk, regularly use a sunscreen with a Broad Sp- ectrum SPF value of 15 or higher and other sun protection measures including:
* limit time in the sun, especially from 10 am to 2 pm
* wear long-sleeved shirts, pants, hats, and sunglasses
■ Children under 6 months of age: ask a doctor

Inactive ingredients

WATER\AQUA\EAU, CYCLOPENTASILOXANE, PROPANEDIOL, BUTYLENE GLYCOL DICAPRYLATE/DI-CAPRATE, LAURYL POLYGLYCERYL-3 POLYDIMETHYLSILOXYETHYL DIMETHICONE, METHYL METHACRYLATE CROSSPOLYMER, BUTYLOCTYL SALICYLATE, CAPRYLYL METHICONE, MAGNESIUM SULFATE, DISTEARDIMONIUM HECTORITE, 1,2-HEXANEDIOL, STEARIC ACID, POLYGLYCERYL-3 POLYDIMETHYLSILOXYETHYL DIMETHICONE, TRIETHOXYCAPRYLYLSILANE, SORBITAN CAPRYLATE, GLYCERYL CAPRYLATE, ETHYLHEXYLGLYCERIN, CITRUS NOBILIS (MANDARIN ORANGE) PEEL OIL, LITSEA CUBEBA FRUIT OIL, CITRUS AURANTIUM DULCIS (ORANGE) OIL, ALUMINUM HYDROXIDE, LIMONENE, CITRAL, TOCOPHEROL <ILN50931>

Other information

Protect the product in this container from excessive heat and direct sunlight

PACKAGE LABEL

Every Sun Day

Mineral Sunscreen

UVA/UVB Protection

Broad Spectrum

SPF 50+

Sunscreen

50mL / 1.69 fl. oz.